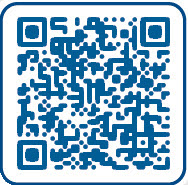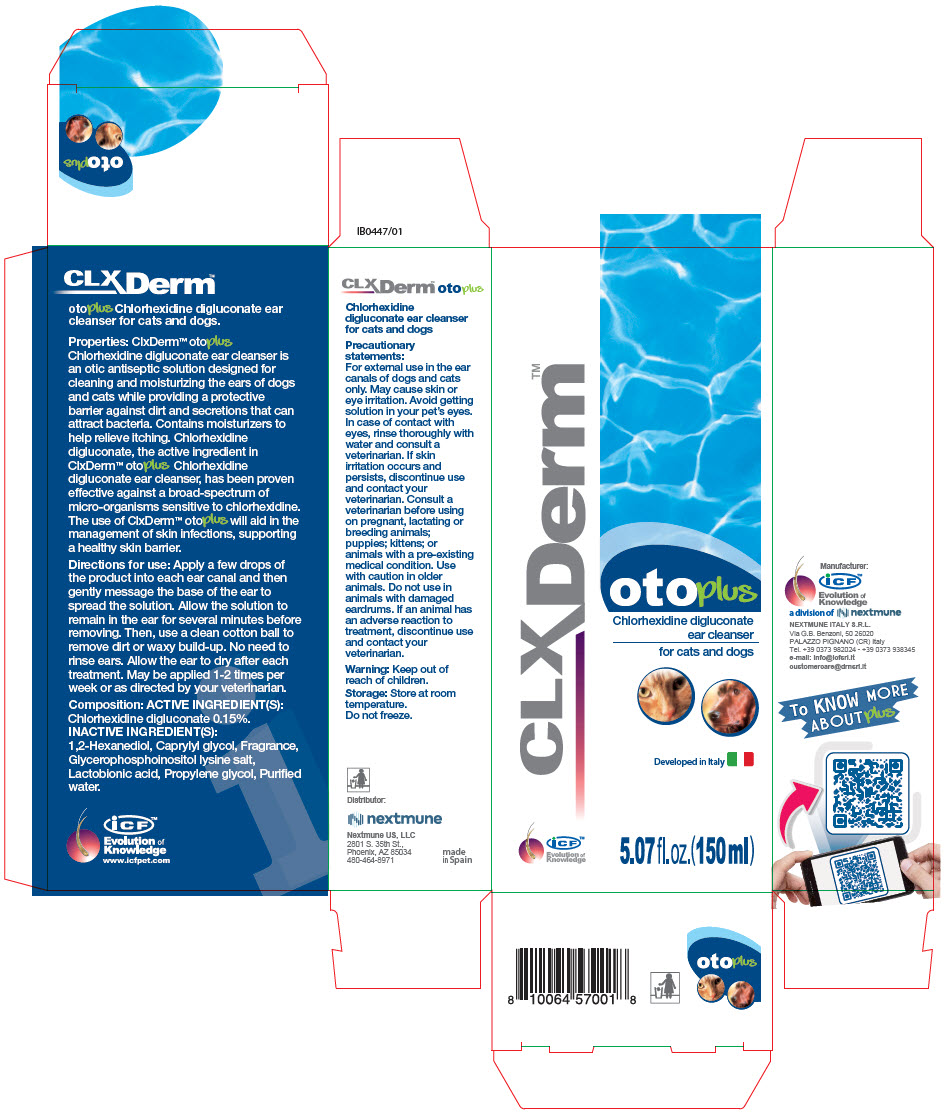 DRUG LABEL: CLX DERM OTO PLUS
NDC: 86127-002 | Form: SOLUTION
Manufacturer: Nextmune AB
Category: animal | Type: OTC ANIMAL DRUG LABEL
Date: 20220419

ACTIVE INGREDIENTS: CHLORHEXIDINE GLUCONATE 1.5 mg/1 mL
INACTIVE INGREDIENTS: water; GLYCEROPHOSPHOINOSITOL LYSINE; PROPYLENE GLYCOL; LACTOBIONIC ACID; CAPRYLYL GLYCOL; 1,2-HEXANEDIOL

CLXDerm™ oto plus

VETERINARY INDICATIONS

oto plus Chlorhexidine digluconate ear cleanser for cats and dogs.

Properties: ClxDerm™ oto plus Chlorhexidine digluconate ear cleanser is an otic antiseptic solution designed for cleaning and moisturizing the ears of dogs and cats while providing a protective barrier against dirt and secretions that can attract bacteria. Contains moisturizers to help relieve itching. Chlorhexidine digluconate, the active ingredient in ClxDerm™ oto plus Chlorhexidine digluconate ear cleanser, has been proven effective against a broad-spectrum of micro-organisms sensitive to chlorhexidine. The use of ClxDerm™ oto plus will aid in the management of skin infections, supporting a healthy skin barrier.

DOSAGE AND ADMINISTRATION

Directions for use: Apply a few drops of the product into each ear canal and then gently message the base of the ear to spread the solution. Allow the solution to remain in the ear for several minutes before removing. Then, use a clean cotton ball to remove dirt or waxy build-up. No need to rinse ears. Allow the ear to dry after each treatment. May be applied 1-2 times per week or as directed by your veterinarian.

Composition:

ACTIVE INGREDIENT(S):

Chlorhexidine digluconate 0.15%.

INACTIVE INGREDIENT(S):

1,2-Hexanediol, Caprylyl glycol, Fragrance, Glycerophosphoinositol lysine salt, Lactobionic acid, Propylene glycol, Purified water.

PRECAUTIONS

Precautionary statements:

For external use in the ear canals of dogs and cats only. May cause skin or eye irritation. Avoid getting solution in your pet's eyes. In case of contact with eyes, rinse thoroughly with water and consult a veterinarian. If skin irritation occurs and persists, discontinue use and contact your veterinarian. Consult a veterinarian before using on pregnant, lactating or breeding animals; puppies; kittens; or animals with a pre-existing medical condition. Use with caution in older animals. Do not use in animals with damaged eardrums. If an animal has an adverse reaction to treatment, discontinue use and contact your veterinarian.

Warning: Keep out of reach of children.

Storage: Store at room temperature.

Do not freeze.

www.icfpet.com

Distributor:
Nextmune US, LLC
2801 S. 35th St.,
Phoenix, AZ 85034
480-464-8971

made
in Spain

Manufacturer:
iCF™
Evolution of
Knowledge
a division of
NEXTMUNE ITALY S.R.L.
Via G.B. Benzoni, 50 26020
PALAZZO PIGNANO (CR) Italy
Tel. +39 0373 982024
+39 0373 938345
e-mail: info@icfsrl.it
customercare@drnsrl.it

To KNOW MORE
ABOUT plus

PRINCIPAL DISPLAY PANEL - 150 ml Bottle Carton

CLXDerm™

oto plus

Chlorhexidine digluconate
ear cleanser
for cats and dogs

Developed in Italy

iCF™

Evolution of
Knowledge

5.07 fl. oz.(150 ml)